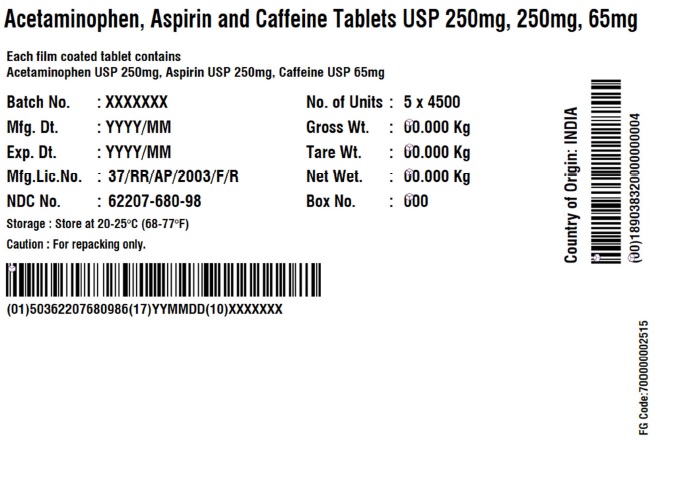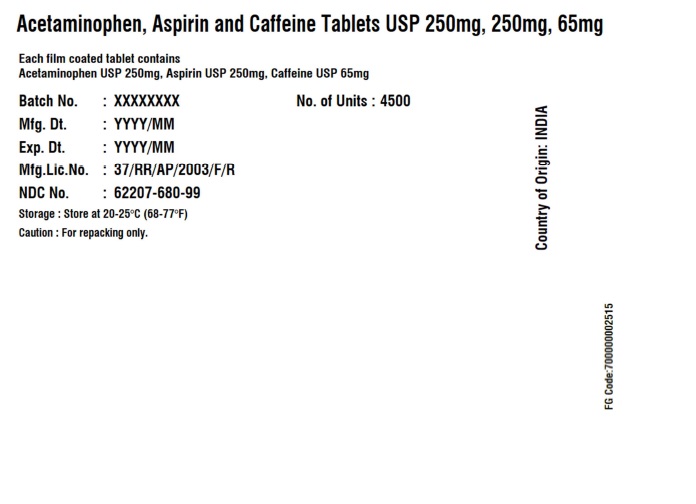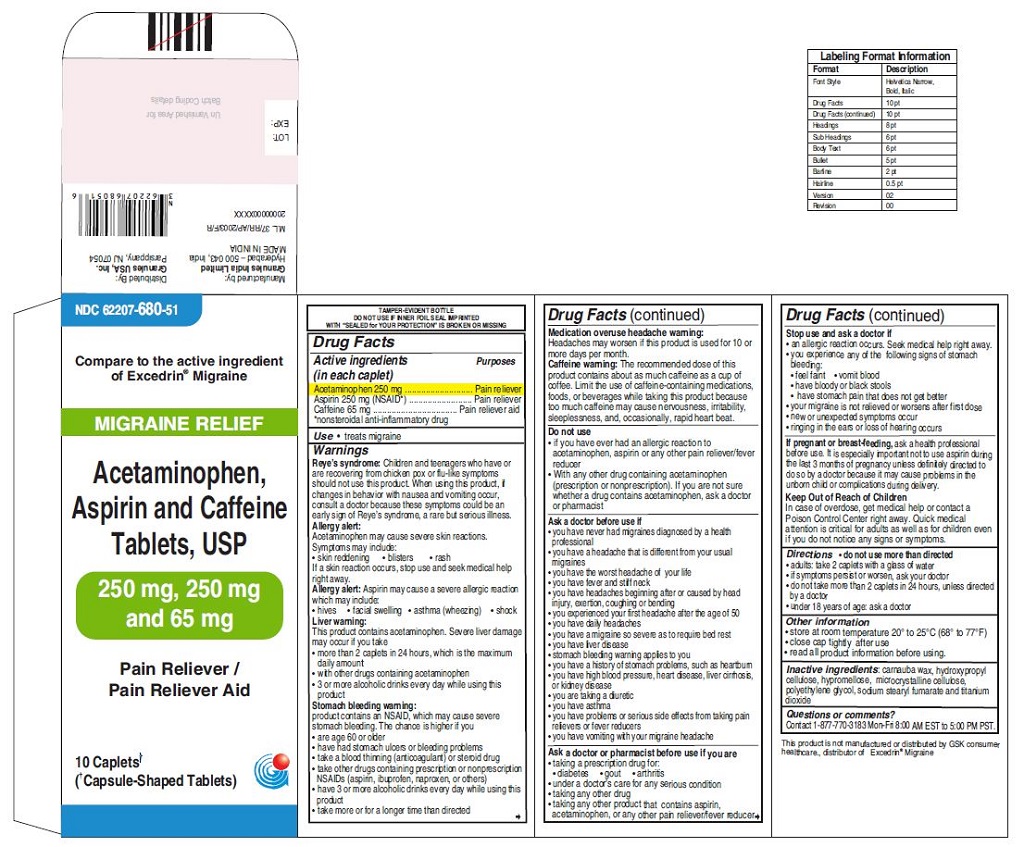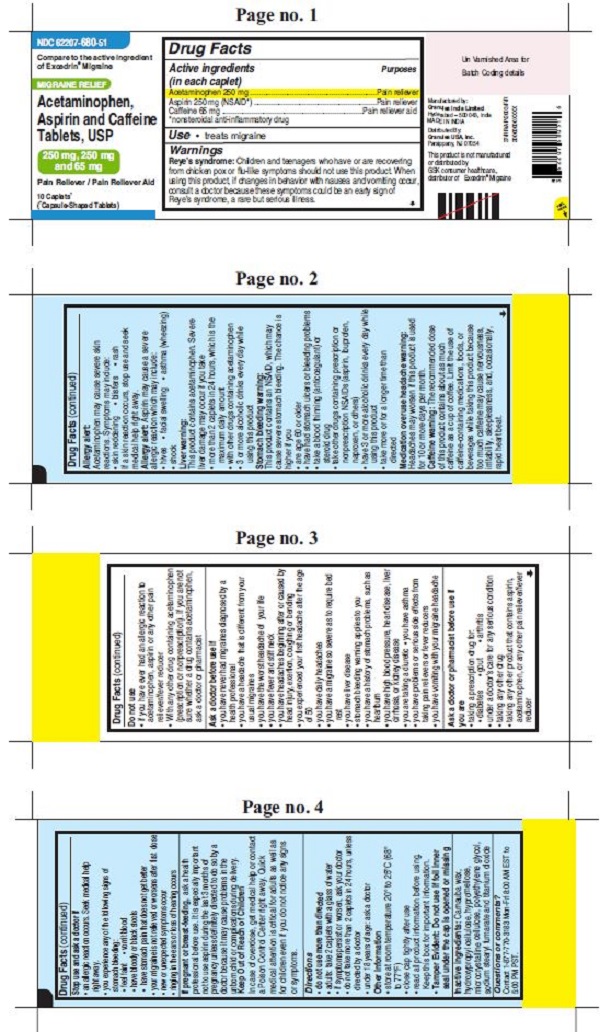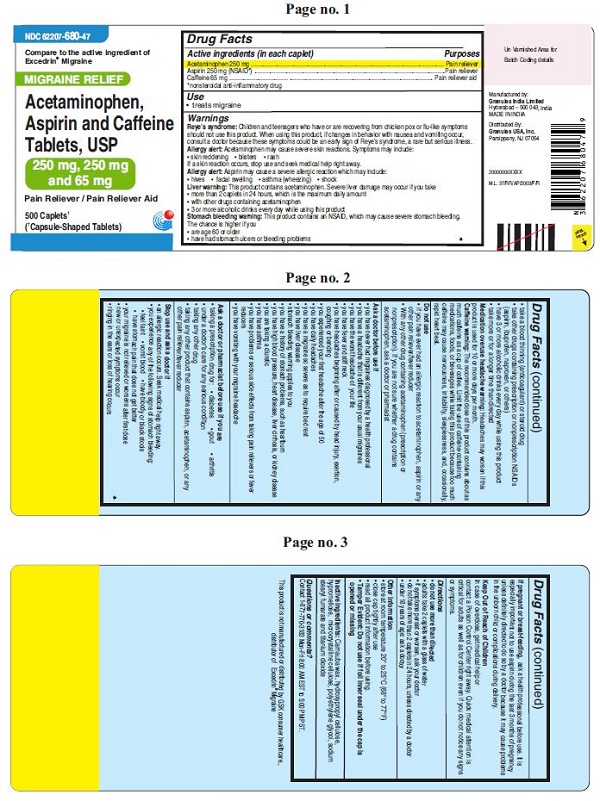 DRUG LABEL: Acetaminophen, Aspirin and Caffeine
NDC: 62207-680 | Form: TABLET
Manufacturer: Granules India Ltd
Category: otc | Type: HUMAN OTC DRUG LABEL
Date: 20251201

ACTIVE INGREDIENTS: ACETAMINOPHEN 250 mg/1 1; ASPIRIN 250 mg/1 1; CAFFEINE 65 mg/1 1
INACTIVE INGREDIENTS: SODIUM STEARYL FUMARATE; POLYETHYLENE GLYCOL 400; MICROCRYSTALLINE CELLULOSE; CARNAUBA WAX; TITANIUM DIOXIDE; HYDROXYPROPYL CELLULOSE (110000 WAMW); HYPROMELLOSE 2910 (6 MPA.S)

Acetaminophen, Aspirin and Caffeine Tablets USP, 250 mg, 250 mg and 65 mg

ACTIVE INGREDIENT(S)

Acetaminophen 250 mg
Aspirin 250 mg (NSAID*)
Caffeine 65 mg
*nonsteroidal anti-inflammatory drug

PURPOSE

Pain reliever
Pain reliever
Pain reliever aid

USE(S)

- treats migraine

WARNINGS

Reye’s syndrome: Children and teenagers who have or are recovering from chicken pox or flu-like symptoms should not use this product. When using this product, if changes in behavior with nausea and vomiting occur, consult a doctor because these symptoms could be an early sign of Reye’s syndrome, a rare but serious illness.
Allergy alert: Acetaminophen may cause severe skin reactions. Symptoms may include:
• skin reddening
• blisters
• rash
If a skin reaction occurs, stop use and seek medical help right away.

Allergy alert: Aspirin may cause a severe allergic reaction which may include:
• hives
• facial swelling
• asthma (wheezing)
• shock

Liver warning: This product contains acetaminophen. Severe liver damage may occur if you take
• more than 2 caplets in 24 hours, which is the maximum daily amount
• with other drugs containing acetaminophen
• 3 or more alcoholic drinks every day while using this product

Stomach bleeding warning: This product contains an NSAID, which may cause severe stomach bleeding. The chance is higher if you
• are age 60 or older
• have had stomach ulcers or bleeding problems
• take a blood thinning (anticoagulant) or steroid drug
• take other drugs containing prescription or nonprescription NSAIDs (aspirin, ibuprofen, naproxen, or others)
• have 3 or more alcoholic drinks every day while using this product
• take more or for a longer time than directed

Medication overuse headache warning: Headaches may worsen if this product is used for 10 or more days per month

Caffeine warning: The recommended dose of this product contains about as much caffeine as a cup of coffee. Limit the use of caffeine-containing medications, foods, or beverages while taking this product because too much caffeine may cause nervousness, irritability, sleeplessness, and, occasionally, rapid heart beat.

DO NOT USE

• if you have ever had an allergic reaction to acetaminophen, aspirin or any other pain reliever/fever reducer
• with any other drug containing acetaminophen (prescription or nonprescription). If you are not sure whether a drug contains acetaminophen, ask a doctor or pharmacist

ASK A DOCTOR BEFORE USE IF

• you have never had migraines diagnosed by a health professional
• you have a headache that is different from your usual migraines
• you have the worst headache of your life
• you have fever and stiff neck
• you have headaches beginning after or caused by head injury, exertion, coughing or bending
• you experienced your first headache after the age of 50
• you have daily headaches
• you have a migraine so severe as to require bed rest
• you have liver disease
• stomach bleeding warning applies to you
• you have a history of stomach problems, such as heartburn
• you have high blood pressure, heart disease, liver cirrhosis, or kidney disease
• you are taking a diuretic
• you have asthma
• you have problems or serious side effects from taking pain relievers or fever reducers
• you have vomiting with your migraine headache

ASK A DOCTOR OR PHARMACIST BEFORE USE IF

• taking a prescription drug for:
o diabetes
o gout
o arthritis
• under a doctor’s care for any serious condition
• taking any other drug
• taking any other product that contains aspirin, acetaminophen, or any other pain reliever/fever reducer

STOP USE AND ASK DOCTOR IF

• an allergic reaction occurs. Seek medical help right away.
• you experience any of the following signs of stomach bleeding :
o feel faint
o vomit blood
o have bloody or black stools
o have stomach pain that does not get better
• your migraine is not relieved or worsens after first dose
• new or unexpected symptoms occur
• ringing in the ears or loss of hearing occurs

IF PREGNANT OR BREAST FEEDING

Ask a health professional before use. It is especially important not to use aspirin during the last 3 months of pregnancy unless definitely directed to do so by a doctor because it may cause problems in the unborn child or complications during delivery.

KEEP OUT OF REACH OF CHILDREN

In case of overdose, get medical help or contact a Poison Control Center right away. Quick medical attention is critical for adults as well as for children even if you do not notice any signs or symptoms.

DIRECTIONS

• do not use more than directed
• adults: take 2 caplets with a glass of water
• if symptoms persist or worsen, ask your doctor
• do not take more than 2 caplets in 24 hours, unless directed by a doctor
• under 18 years of age: ask a doctor

OTHER INFORMATION

• store at controlled room temperature 20° to 25°C (68° to 77°F)
• close cap tightly after use
• read all product information before using. Keep this box for important information.

• Tamper Evident : Do not use if foil inner seal under the cap is opened or missing

INACTIVE INGREDIENTS

Carnauba wax, hydroxypropyl cellulose, hypromellose, microcrystalline cellulose, propylene glycol, sodium stearyl fumarate and titanium dioxide

QUESTIONS OR COMMENTS?

Contact 1-877-770-3183 Mon-Fri 8:00 AM EST to 5:00 PM PST
Manufactured by:
Granules India Limited
Hyderabad-500 043, India
MADE IN INDIA
Distributed By:
Granules USA, Inc.
Parsippany, NJ 07054